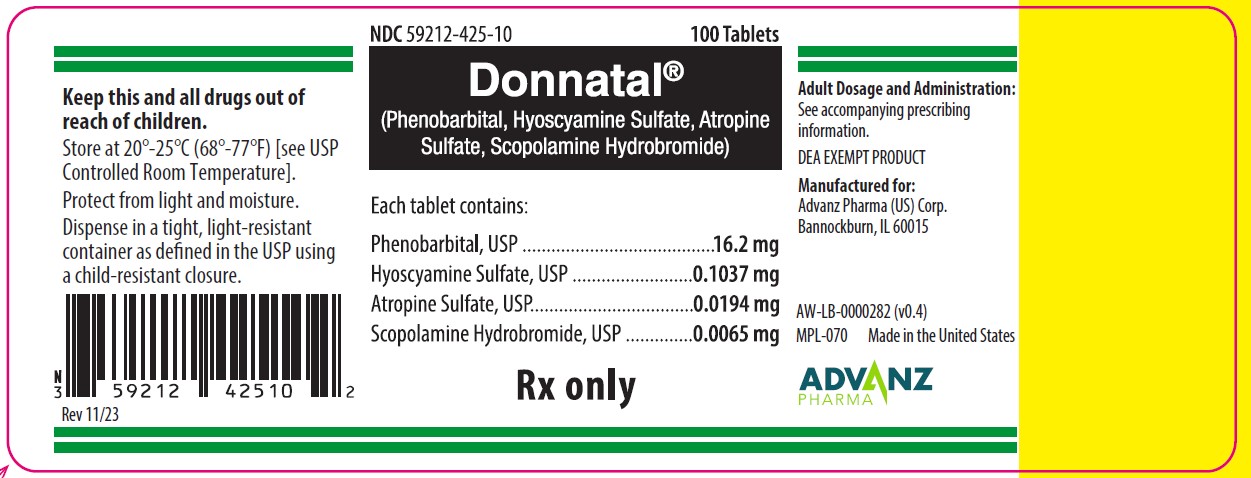 DRUG LABEL: Donnatal
NDC: 59212-425 | Form: TABLET
Manufacturer: Advanz Pharma (US) Corp.
Category: prescription | Type: Human Prescription Drug Label
Date: 20241205
DEA Schedule: CIV

ACTIVE INGREDIENTS: PHENOBARBITAL 16.2 mg/1 1; HYOSCYAMINE SULFATE 0.1037 mg/1 1; ATROPINE SULFATE 0.0194 mg/1 1; SCOPOLAMINE HYDROBROMIDE 0.0065 mg/1 1
INACTIVE INGREDIENTS: DIBASIC CALCIUM PHOSPHATE DIHYDRATE; SUCROSE; MICROCRYSTALLINE CELLULOSE; STARCH, CORN; STEARIC ACID; SILICON DIOXIDE; MAGNESIUM STEARATE

DONNATAL® (Phenobarbital, Hyoscyamine Sulfate, Atropine Sulfate, Scopolamine Hydrobromide) Tablets
Rx Only
Revised: 11/23

DESCRIPTION

Donnatal® Tablets

Each Donnatal® Tablet contains:

Phenobarbital, USP..................................... 16.2 mg
Hyoscyamine Sulfate, USP...................... 0.1037 mg
Atropine Sulfate, USP .............................0.0194 mg
Scopolamine Hydrobromide, USP ...........0.0065 mg

Inactive Ingredients

Dibasic Calcium Phosphate Dihydrate, Compressible Sugar, Microcrystalline Cellulose, Sodium Starch Glycolate, Stearic Acid, Silicon Dioxide Colloidal, Magnesium Stearate.

CLINICAL PHARMACOLOGY

This drug combination provides natural belladonna alkaloids in a specific, fixed ratio combined with phenobarbital to provide peripheral anticholinergic/antispasmodic action and mild sedation.

INDICATIONS AND USAGE
Based on a review of this drug by the National Academy of Sciences-National Research Council and/or other information, FDA has classified the indications as follows: "Possibly" effective: For use as adjunctive therapy in the treatment of irritable bowel syndrome (irritable colon, spastic colon, mucous colitis) and acute enterocolitis.
May also be useful as adjunctive therapy in the treatment of duodenal ulcer.
Final classification of the less-than-effective indications requires further investigation.
IT HAS NOT BEEN SHOWN CONCLUSIVELY WHETHER ANTICHOLINERGIC/ANTISPASMODIC DRUGS AID IN THE HEALING OF A DUODENAL ULCER, DECREASE THE RATE OF RECURRENCES OR PREVENT COMPLICATIONS.

CONTRAINDICATIONS

- glaucoma;
- obstructive uropathy (for example, bladder neck obstruction due to prostatic hypertrophy);
- obstructive disease of the gastrointestinal tract (as in achalasia, pyloroduodenal stenosis, etc.);
- paralytic ileus, intestinal atony of the elderly or debilitated patient;
- unstable cardiovascular status in acute hemorrhage;
- severe ulcerative colitis especially if complicated by toxic megacolon;
- myasthenia gravis;
- hiatal hernia associated with reflux esophagitis;
- in patients with known hypersensitivity to any of the ingredients.

Phenobarbital is contraindicated in acute intermittent porphyria and in those patients in whom phenobarbital produces restlessness and/or excitement.

WARNINGS

Donnatal® Tablets can cause fetal harm when administered to a pregnant woman. Animal reproduction studies have not been conducted with Donnatal® Tablets. If this drug is used during pregnancy, or if the patient becomes pregnant while taking this drug, the patient should be apprised of the potential hazard to the fetus.

In the presence of a high environmental temperature, heat prostration can occur with belladonna alkaloids (fever and heatstroke due to decreased sweating).

Diarrhea may be an early symptom of incomplete intestinal obstruction, especially in patients with ileostomy or colostomy. In this instance, treatment with this drug would be inappropriate and possibly harmful.

Donnatal® Tablets may produce drowsiness or blurred vision. The patient should be warned, should these occur, not to engage in activities requiring mental alertness, such as operating a motor vehicle or other machinery, and not to perform hazardous work.

Phenobarbital may decrease the effect of anticoagulants, and necessitate larger doses of the anticoagulant for optimal effect. When the phenobarbital is discontinued, the dose of the anticoagulant may have to be decreased.

Phenobarbital may be habit forming and should not be administered to individuals known to be addiction prone or to those with a history of physical and/or psychological dependence upon drugs.

Since barbiturates are metabolized in the liver, they should be used with caution and initial doses should be small in patients with hepatic dysfunction.

PRECAUTIONS

General

Use with caution in patients with:

- autonomic neuropathy
- hepatic or renal disease
- hyperthyroidism
- coronary heart disease
- congestive heart failure
- cardiac arrhythmias
- tachycardia
- hypertension

Belladonna alkaloids may produce a delay in gastric emptying (antral stasis) which would complicate the management of gastric ulcer.

Do not rely on the use of the drug in the presence of complication of biliary tract disease.

Theoretically, with overdosage, a curare-like action may occur.

Information for Patients

Donnatal® Tablets may produce drowsiness or blurred vision. The patient should be warned, should these occur, not to engage in activities requiring mental alertness, such as operating a motor vehicle or other machinery, and not to perform hazardous work.

Drug Interactions

Phenobarbital may decrease the effect of anticoagulants, and necessitate larger doses of the anticoagulant for optimal effect. When the phenobarbital is discontinued, the dose of the anticoagulant may have to be decreased.

Carcinogenesis, Mutagenesis, Impairment of Fertility

Long-term studies in animals have not been performed to evaluate carcinogenic potential.

Pregnancy

Animal reproduction studies have not been conducted with Donnatal® Tablets. There is positive evidence of human fetal risk based on adverse reaction data from investigational or marketing experience or studies in humans, but potential benefits may warrant use of the drug in pregnant women despite potential risks (see WARNINGS).

Nursing Mothers

It is not known whether this drug is excreted in human milk. Because many drugs are excreted in human milk, caution should be exercised when Donnatal® Tablets are administered to a nursing woman.

Geriatric Use

Elderly patients may react with symptoms of excitement, agitation, drowsiness, and other untoward manifestations to even small doses of the drug.

ADVERSE REACTIONS

Adverse reactions may include xerostomia; urinary hesitancy and retention; blurred vision; tachycardia; palpitation; mydriasis; cycloplegia; increased ocular tension; loss of taste sense; headache; nervousness; drowsiness; weakness; dizziness; insomnia; nausea; vomiting; impotence; suppression of lactation; constipation; bloated feeling; musculoskeletal pain; severe allergic reaction or drug idiosyncrasies, including anaphylaxis, urticaria, and other dermal manifestations; and decreased sweating.

Acquired hypersensitivity to barbiturates consists chiefly in allergic reactions that occur especially in persons who tend to have asthma, urticaria, angioedema, and similar conditions. Hypersensitivity reactions in this category include localized swelling, particularly of the eyelids, cheeks, or lips, and erythematous dermatitis. Rarely, exfoliative dermatitis (e.g. Stevens-Johnson syndrome and toxic epidermal necrolysis) may be caused by phenobarbital and can prove fatal. The skin eruption may be associated with fever, delirium, and marked degenerative changes in the liver and other parenchymatous organs. In a few cases, megaloblastic anemia has been associated with the chronic use of phenobarbital.

Phenobarbital may produce excitement in some patients, rather than a sedative effect.

To report SUSPECTED ADVERSE REACTIONS, contact Advanz Pharma (US) Corp. at 1-877-370-1142 or FDA at 1-800-FDA-1088 or www.fda.gov/medwatch.

DRUG ABUSE AND DEPENDENCE

Abuse

Phenobarbital may be habit forming and should not be administered to individuals known to be addiction prone or to those with a history of physical and/or psychological dependence upon drugs (see WARNINGS).

Dependence

In patients habituated to barbiturates, abrupt withdrawal may produce delirium or convulsions.

OVERDOSAGE

The signs and symptoms of overdose are headache, nausea, vomiting, blurred vision, dilated pupils, hot and dry skin, dizziness, dryness of the mouth, difficulty in swallowing, and CNS stimulation. Treatment should consist of gastric lavage, emetics, and activated charcoal. If indicated, parenteral cholinergic agents such as physostigmine or bethanechol chloride should be used.

DOSAGE AND ADMINISTRATION

The dosage of Donnatal® Tablets should be adjusted to the needs of the individual patient to assure symptomatic control with a minimum of adverse effects.

Donnatal® Tablets - Adults: One or two Donnatal® Tablets three or four times a day according to condition and severity of symptoms.

HOW SUPPLIED

Donnatal® Tablets are supplied as: white, D-shaped, flat faced beveled edge tablets embossed "D" on one side and debossed "Donnatal" on the other side.

- Bottles of 100 tablets - NDC 59212-425-10.
- Bottles of 4 tablets - NDC 59212-425-04.

Store at 20°-25°C (68°-77°F) [See USP Controlled Room Temperature]. Protect from light and moisture.

Dispense in a tight, light-resistant container as defined in the USP using a child-resistant closure.
DEA EXEMPT PRODUCT
Manufactured for:
Advanz Pharma (US) Corp.
Bannockburn, IL 60015

DONNATAL® is a registered trademark of Mercury Pharma Group Limited.
Distributed by Advanz Pharma (US) Corp. under license

Revised: 11/23

PRINCIPAL DISPLAY PANEL

NDC 59212-425-10 100 Tablets

Donnatal®
(Phenobarbital, Hyoscyamine Sulfate, Atropine Sulfate, Scopolamine Hydrobromide)

Each tablet contains:

Phenobarbital, USP..................................... 16.2 mg
Hyoscyamine Sulfate, USP...................... 0.1037 mg
Atropine Sulfate, USP .............................0.0194 mg
Scopolamine Hydrobromide, USP ...........0.0065 mg

Rx only